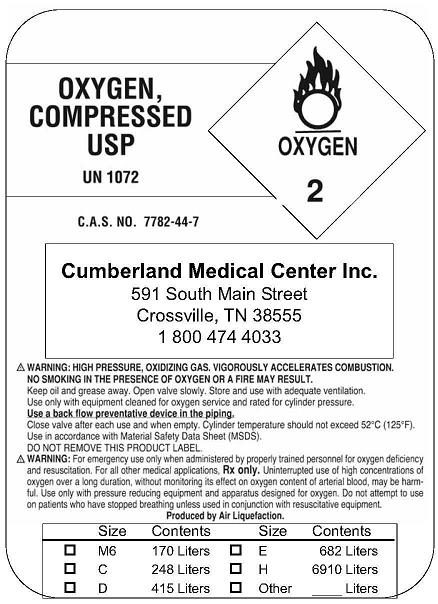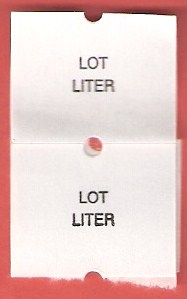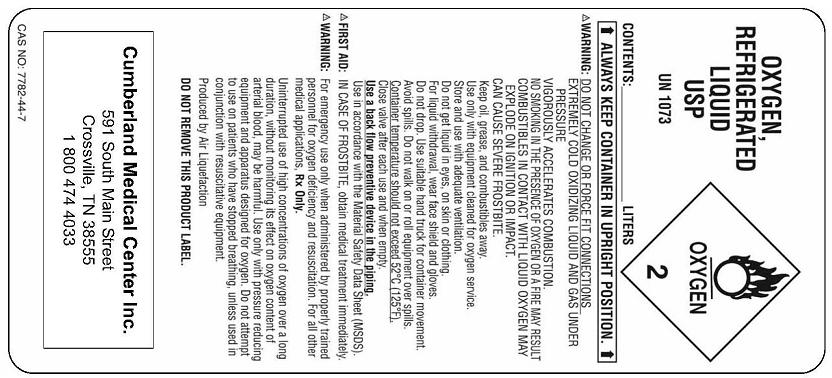 DRUG LABEL: Oxygen
NDC: 53742-001 | Form: GAS
Manufacturer: Cumberland Medical Center- Medical Equipment Services
Category: prescription | Type: HUMAN PRESCRIPTION DRUG LABEL
Date: 20091221

ACTIVE INGREDIENTS: Oxygen 99 L/100 L

Oxygen